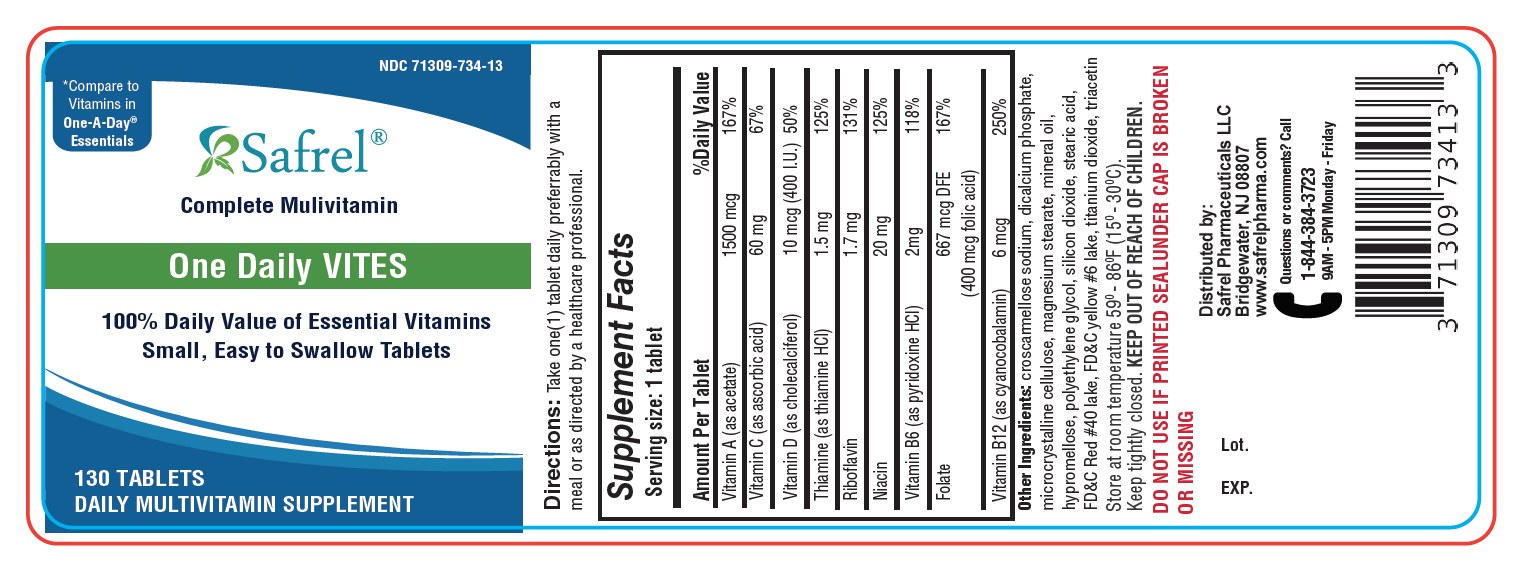 DRUG LABEL: One Daily VITES
NDC: 71309-734 | Form: TABLET
Manufacturer: Safrel Pharmaceuticals, LLC.
Category: other | Type: DIETARY SUPPLEMENT
Date: 20210312

ACTIVE INGREDIENTS: VITAMIN A ACETATE 5000 [iU]/1 1; ASCORBIC ACID 60 mg/1 1; CHOLECALCIFEROL 400 [iU]/1 1; THIAMINE HYDROCHLORIDE 1.5 mg/1 1; RIBOFLAVIN 1.7 mg/1 1; NIACIN 20 mg/1 1; PYRIDOXINE HYDROCHLORIDE 2 mg/1 1; Folic acid 0.4 mg/1 1; CYANOCOBALAMIN 6 ug/1 1
INACTIVE INGREDIENTS: ANHYDROUS DIBASIC CALCIUM PHOSPHATE; stearic acid; microcrystalline cellulose; HYPROMELLOSE, UNSPECIFIED; croscarmellose sodium; FD&C RED NO. 40; mineral oil; POLYETHYLENE GLYCOL, UNSPECIFIED; titanium dioxide; triacetin; SILICON DIOXIDE; MAGNESIUM STEARATE; FD&C YELLOW NO. 6

One Daily VITES

DO NOT USE IF PRINTED SEALUNDER CAP IS BROKEN OR MISSING

DIRECTIONS

Take one(1) tablet daily preferrably with a meal or as directed by a healthcare professional.

STATEMENT OF IDENTITY

Supplement Facts
Serving Size 1 Tablet
Amount per tablet |  | % Daily Value
Vitamin A (as acetate) | 5000 IU | 100%
Vitamin C (as ascorbic acid) | 60 mg | 100%
Vitamin D-3 (as cholecalciferol) | 400 IU | 100%
Vitamin B-1 (as thiamine HCl) | 1.5 mg | 100%
Vitamin B-2 (riboflavin) | 1.7 mg | 100%
Niacin (as Vitamin B-3) | 20 mg | 100%
Vitamin B-6 (as pyridoxine HCl) | 2 mg | 100%
Folic Acid | 0.4 mg | 100%
Vitamin B-12 (as cyanocobalamin) | 6 mcg | 100%

Other Ingredients: croscarmellose sodium, dicalcium phosphate, microcrystalline cellulose, magnesium stearate, mineral oil, hypromellose, polyethylene glycol, silicon dioxide, stearic acid, FD&C Red #40 lake, FD&C yellow #6 lake, titanium dioxide, triacetin

HEALTH CLAIM

Store between 15° - 30°C (59° - 86°F). Keep tightly closed. KEEP OUT OF REACH OF CHILDREN.

HEALTH CLAIM

Distributed by:

Safrel Pharmaceuticals

Bridgewater, NJ 088807

www.safrel.com

Questions or comments?
1-844-384-3723

www.safrel.com

Lot.

Exp.